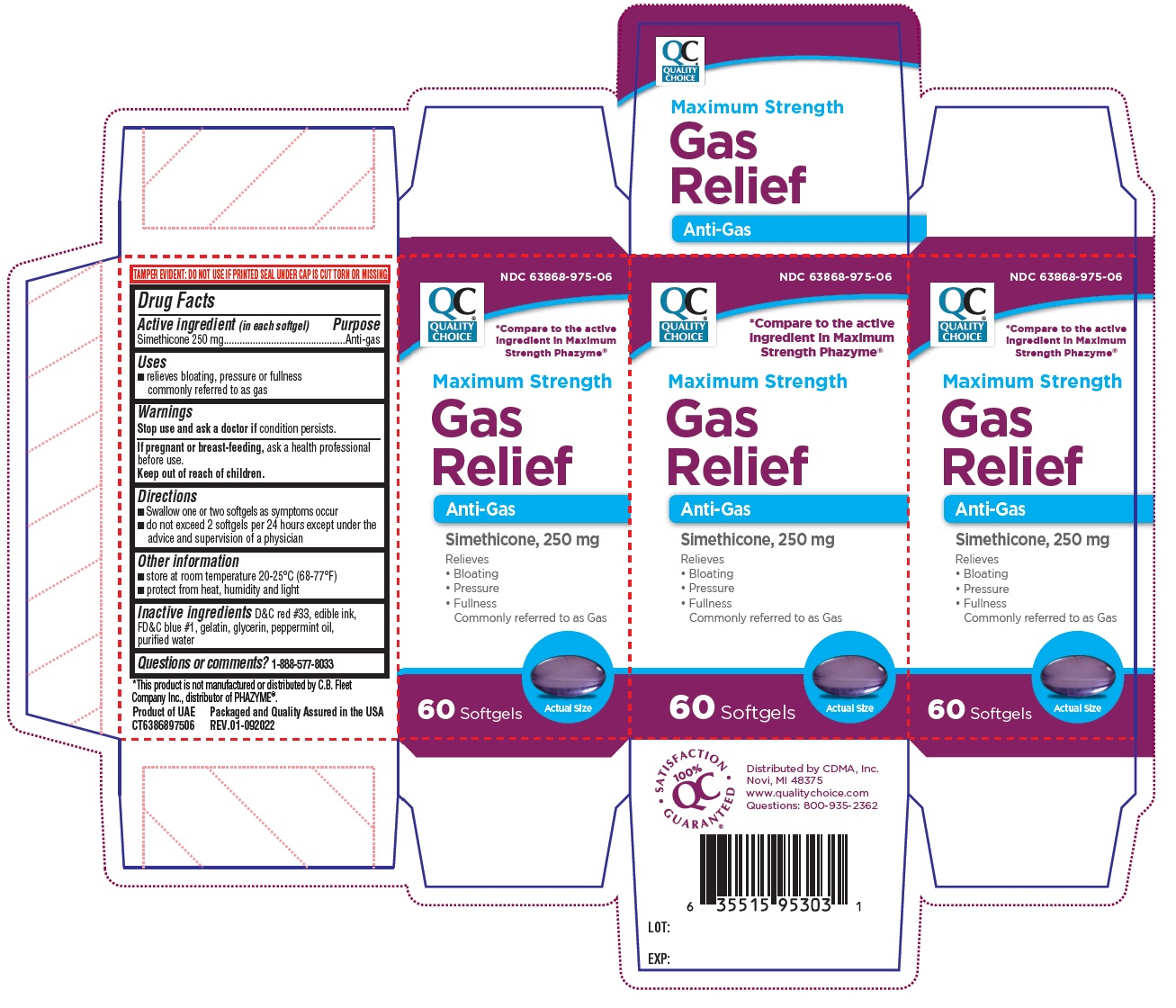 DRUG LABEL: Maximum Strength Gas Relief
NDC: 63868-975 | Form: CAPSULE, LIQUID FILLED
Manufacturer: Chain Drug Marketing Association, Inc.
Category: otc | Type: HUMAN OTC DRUG LABEL
Date: 20241216

ACTIVE INGREDIENTS: DIMETHICONE, UNSPECIFIED 250 mg/1 1
INACTIVE INGREDIENTS: D&C RED NO. 33; FD&C BLUE NO. 1; GELATIN, UNSPECIFIED; GLYCERIN; PEPPERMINT OIL; WATER

Maximum Strength Gas Relief

Active ingredient (in each softgel)

Simethicone 250 mg

Purpose

Anti-gas

Uses

- relieves bloating, pressure or fullness commonly referred to as gas

Warnings

Stop use and ask a doctor if condition persists

If pregnant or breast-feeding, ask a health professional before use.

Keep out of reach of children.

Directions

- Swallow one or two softgels as symptoms occur
- do not exceed 2 softgels per 24 hours except under the advice and supervision of a physician

Other information

- store at room temperature 20-25°C (68-77°F)
- protect from heat, humidity and light

Inactive ingredients

D&C red #33, edible ink, FD&C blue #1, gelatin, glycerin, peppermint oil, purified water

Questions or comments?

1-888-577-8033

QUALITY CHOICE

*Compare to the active Ingredient in Maximum Strength Phazyme®

TAMPER EVIDENT: DO NOT USE IF PRINTED SEAL UNDER CAP IS CUT TORN OR MISSING

*This product is not manufactured or distributed by C.B. Fleet Company Inc., distributor of PHAZYME®.

Product of UAE

Packaged and Qualify Assured in the USA

REV.01-092022

QC 100% SATISFACTION GUARANTEED

Distributed by CDMA, Inc.
Novi, MI 48375
www.qualitychoice.com
Questions: 800-935-2362